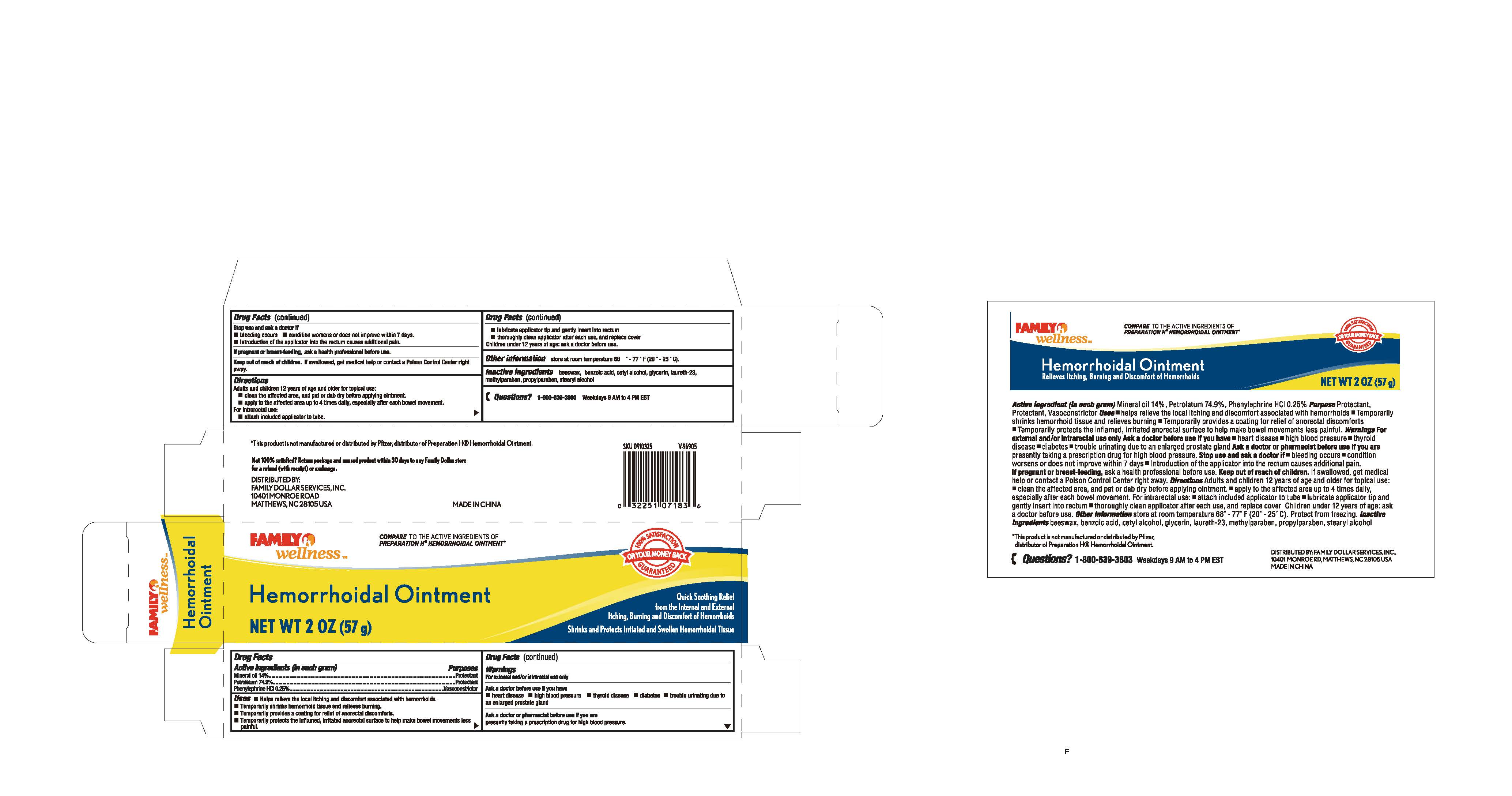 DRUG LABEL: Family wellness
NDC: 69571-006 | Form: OINTMENT
Manufacturer: FRONT PHARMACEUTICAL PLC
Category: otc | Type: HUMAN OTC DRUG LABEL
Date: 20231027

ACTIVE INGREDIENTS: MINERAL OIL 14 g/100 g; PETROLATUM 74.9 g/100 g; PHENYLEPHRINE HYDROCHLORIDE 0.25 g/100 g
INACTIVE INGREDIENTS: YELLOW WAX; BENZOIC ACID; CETYL ALCOHOL; GLYCERIN; LAURETH-23; METHYLPARABEN; PROPYLPARABEN; STEARYL ALCOHOL

Active ingredients (in each gram)

Mineral oil 14%

Petrolatum 74.9%

Phenylephrine HCl 0.25%

Purposes

Protectant

Protectant

Vasoconstrictor

INDICATIONS AND USAGE

•helps relieve the local itching and discomfort associated with hemorrhoids. Uses

•Temporarily shrinks hemorrhoid tissue and relieves burning.

•Temporarily provides a coating for relief of anorectal burning.

•Temporarily protects the inflamed, irritated anorectal surface to help make bowel movements less

painful

Warnings

For external and/or intrarectal use only

Ask a doctor before use if you have

•heart disease •high blood pressure •thyroid disease •diabetes •trouble urinating due to

an enlarged prostate gland

Ask a doctor or pharmacist before use if you are

presently taking a prescription drug for high blood pressure.

Stop use and ask a doctor if

•bleeding occurs •condition worsens or does not improve within 7 days.

•introduction of the applicator into the rectum causes additional pain.

, ask a health professional before use. If pregnant or breast-feeding

KEEP OUT OF REACH OF CHILDREN

If swallowed, get medical help or contact a Poison Control Center right Keep out of reach of children.

away.

Directions

Adults and children 12 years of age and older for topical use:

•clean the affected area, and pat or dab dry before applying ointment.

•apply to the affected area up to 4 times daily, especially after each bowel movement.

For intrarectal use:

•attach included applicator to tube.

•lubricate applicator tip and gently insert into rectum

•thoroughly clean applicator after each use, and replace cover

Children under 12 years of age: ask a doctor before use.

OTHER SAFETY INFORMATION

store at room temperature 68° - 77° F (20°-25° C). Other information

INACTIVE INGREDIENT

beeswax, benzoic acid, cetyl alcohol, glycerin, laureth-23, Inactive ingredients

methylparaben, propylparaben, stearyl alcohol

QUESTIONS

1-800-639-3803 Weekdays 9 AM to 4 PM EST Questions?